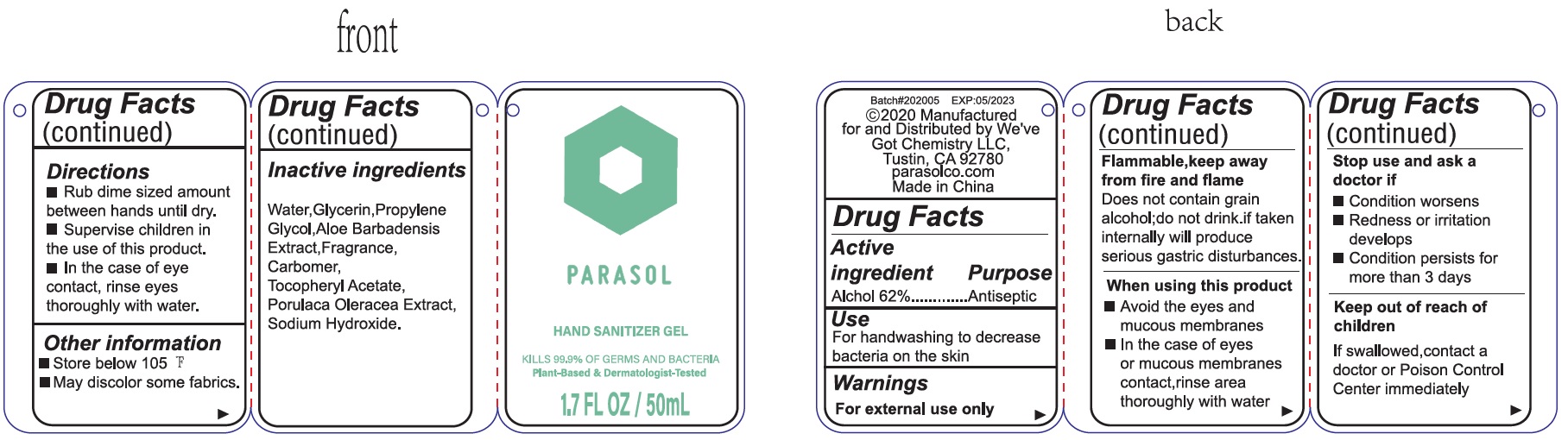 DRUG LABEL: PARASOL HAND SANITIZER
NDC: 77446-000 | Form: GEL
Manufacturer: We've Got Chemistry LLC
Category: otc | Type: HUMAN OTC DRUG LABEL
Date: 20231026

ACTIVE INGREDIENTS: ALCOHOL 0.62 mL/1 mL
INACTIVE INGREDIENTS: WATER; GLYCERIN; PROPYLENE GLYCOL; ALOE VERA LEAF; CARBOMER HOMOPOLYMER, UNSPECIFIED TYPE; .ALPHA.-TOCOPHEROL ACETATE; PURSLANE; SODIUM HYDROXIDE

PARASOL HAND SANITIZER GEL

Active ingredient

Alcohol 62%

Purpose

Antiseptic

Use

- For hand washing to decrease bacteria on the skin

Warnings

For external use only

Flammable, keep away from fire or flame

Does not contain grain alcohol;do not drink .if taken internally will produce serious gastric distrurbances.

When using this product

- Avoid the eyes and mucous membranes
- In the case of eyes or mucous membranes contact,rinse area thoroughly with water

Stop use and ask a doctor if

- Condition worsens
- Redness or irritation develops
- Condition persists for more than 3 days

Keep out of reach of children

if swallowed,contact a doctor or Poison Control Center immediately

Directions

- Rub dime sized amount between hands until dry.
- Supervise children in the use of this product.
- In the case of eye contact, rinse eyes thoroughly with water.

Other information

- Store below 105°F
- May discolor some fabrics.

Inactive ingredients

Water,Glycerin,Propylene Glycol,Aloe Barbadensis Extract,Fragrance,Carbomer, Tocopheryl Acetate, Porulaca Oleracea Extract, Sodium Hydroxide.